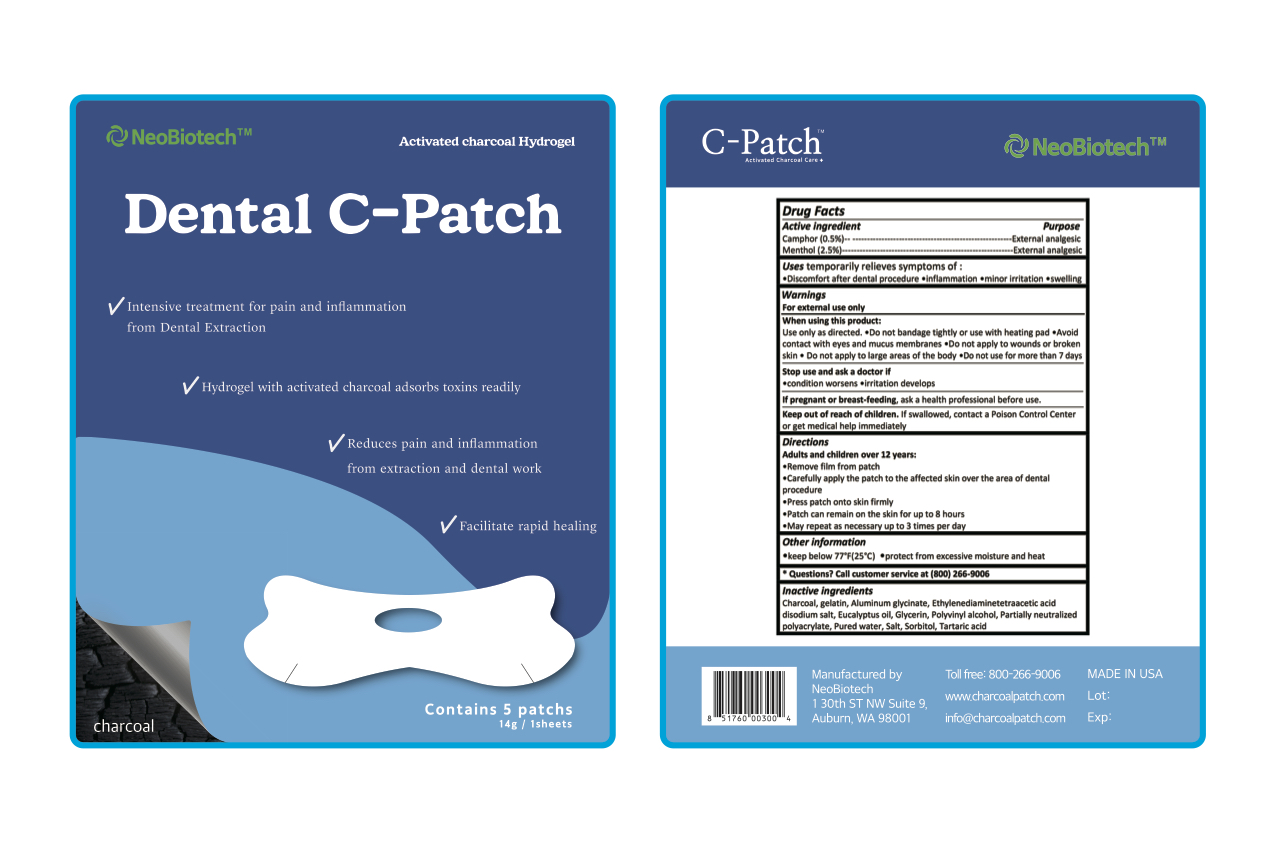 DRUG LABEL: Dental C-Patch
NDC: 70236-104 | Form: PATCH
Manufacturer: NeoBiotech Global Corporation
Category: otc | Type: HUMAN OTC DRUG LABEL
Date: 20180210

ACTIVE INGREDIENTS: CAMPHOR (SYNTHETIC) 0.07 g/14 g; MENTHOL 0.35 g/14 g
INACTIVE INGREDIENTS: EDETIC ACID; ACTIVATED CHARCOAL; DIHYDROXYALUMINUM AMINOACETATE ANHYDROUS; SORBITOL; TARTARIC ACID; GLYCERIN; GELATIN, UNSPECIFIED; EUCALYPTUS OIL; POLYVINYL ALCOHOL, UNSPECIFIED; WATER; SODIUM CHLORIDE

Dental C-Patch

Active ingredients

Camphor (0.5%)

Menthol (2.5%)

Purpose

External analgesic

Uses

temporarily relieves symptoms of

- discomfort after dental procedure

- inflammation

- minor irritation

- swelling

Warnings

For external use only

When using this product

Use only as directed.

- Do not bandage tightly or use with heating pad

- Avoid contact with eyes and mucus membranes

- Do not appy wounds or broken skin

- Do not apply to large areas of the body

- In case of deep or puncture wounds, animal bites or serious burns, consult a doctor

Stop use and ask a doctor if

- condition worsen

- irritation develops

- symptoms persist for more than 7 days or recurs within 1 day of discontinuation

- do not use for more than 7 days

If pregnant or breast-feeding, ask a health professional before use

Keep out of reach of children. If swallowd, contact a Poison Control Center or get medical help immediatel

Directions

Adults and children over 12 years:

- remove film from patch

- carefully apply the patch to the affected skin over the area of ental procedure

- press patch onto skin firmly

- patch can remain on the skin for up to 8 hours

- may repeat as necessary up to 3 times per day

Inactive ingredients

Charcoal, gelatin, Aluminum glycinate, Ethylenediaminetetraacetic acid, disodium slat, eucalyptus oil, glycerin, polyvlnyl alcohol, partially neutralized polyacrytate, pured wter, salt, sorbitol, tartaric acid

Keep out of reach of children. If swallowed, contact a Poison Control Center or get medical help immediately